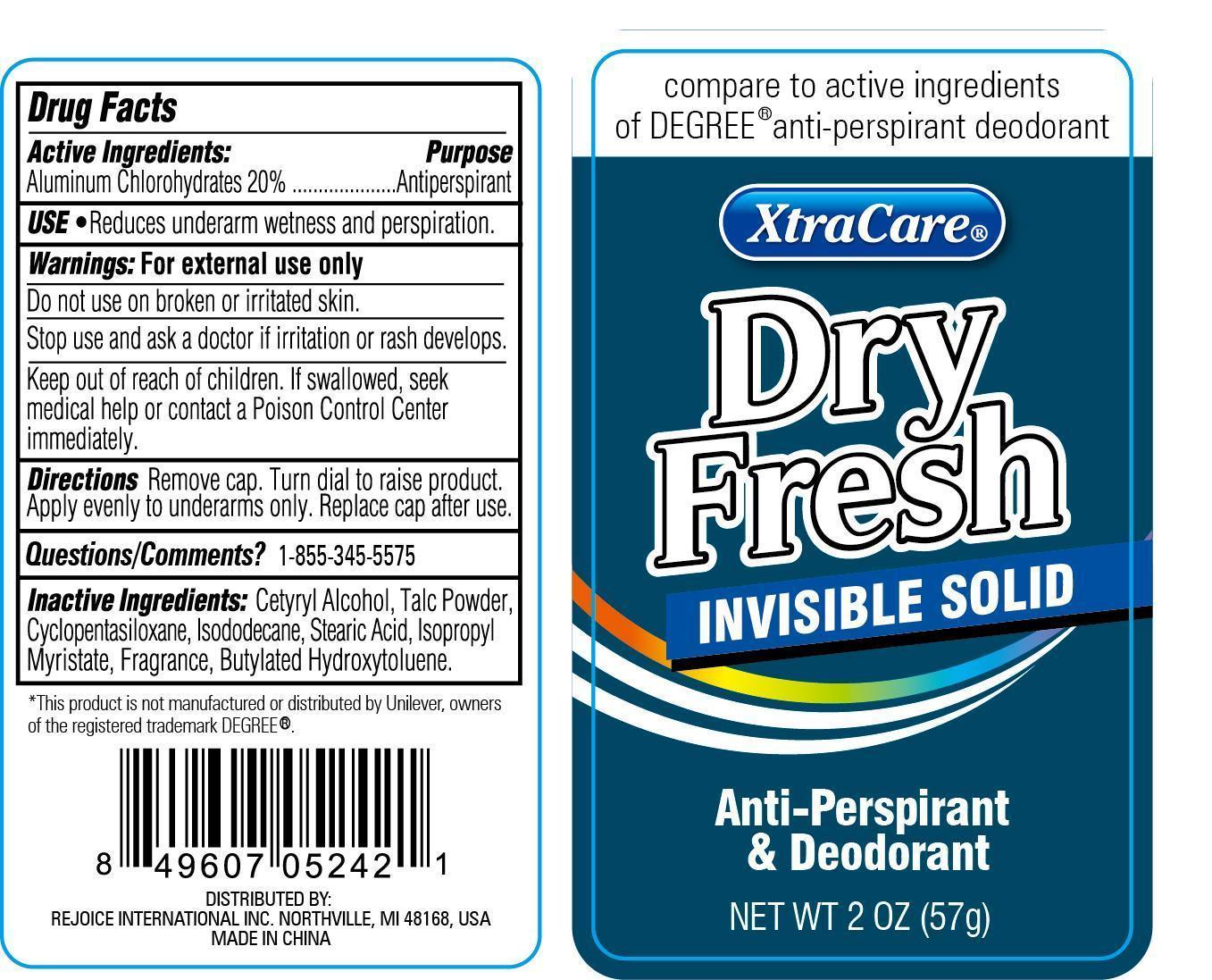 DRUG LABEL: XtraCare Dry Fresh Invisible Solid
NDC: 57337-041 | Form: CREAM
Manufacturer: Rejoice International
Category: otc | Type: HUMAN OTC DRUG LABEL
Date: 20240228

ACTIVE INGREDIENTS: ALUMINUM CHLOROHYDRATE 11 g/57 g
INACTIVE INGREDIENTS: CETYL ALCOHOL; TALC; CYCLOMETHICONE 5; ISODODECANE; STEARIC ACID; ISOPROPYL MYRISTATE; BUTYLATED HYDROXYTOLUENE

XtraCare Dry Fresh Invisible Solid

Active Ingredients Purpose

Aluminum Chlorohydrates 20% ............. Antiperspirant

Uses

Reduces underarm wetness and perspiration.

Keep out of reach of children. If swallowed, get medical help or contact a Poison Control Center immediately.

INDICATIONS AND USAGE

compare to active ingredients of DEGREE® anti-perspirant deodorant

XtraCare® Dry Fresh Invisible Solid

Anti-Perspirant & Deodorant

Net Wt 2 oz (57g)

Warnings: For external use only

Do not use on broken or irritated skin.

Stop use and ask a doctor if irritation or rash develops.

DOSAGE AND ADMINISTRATION

Directions Remove cap. Turn dial to raise product. Apply evenly to underarms only. Replace cap after use.

INACTIVE INGREDIENT

Inactive Ingredients: cetyryl alcohol, talc powder, cyclopentasiloxane, isododecane, stearic acid, isopropyl myristate, fragrance, butylated hydroxytoluene

OTHER SAFETY INFORMATION

Questions/Comments? 1-855-345-5575

*This product is nor manufactured or distributed by Unilever, owners of the registered trade mark DEGREE®

DISTRIBUTED BY:

REJOICE INTERNATIONAL INC, NORTHVILLE, MI 48168 USA

MADE IN CHINA